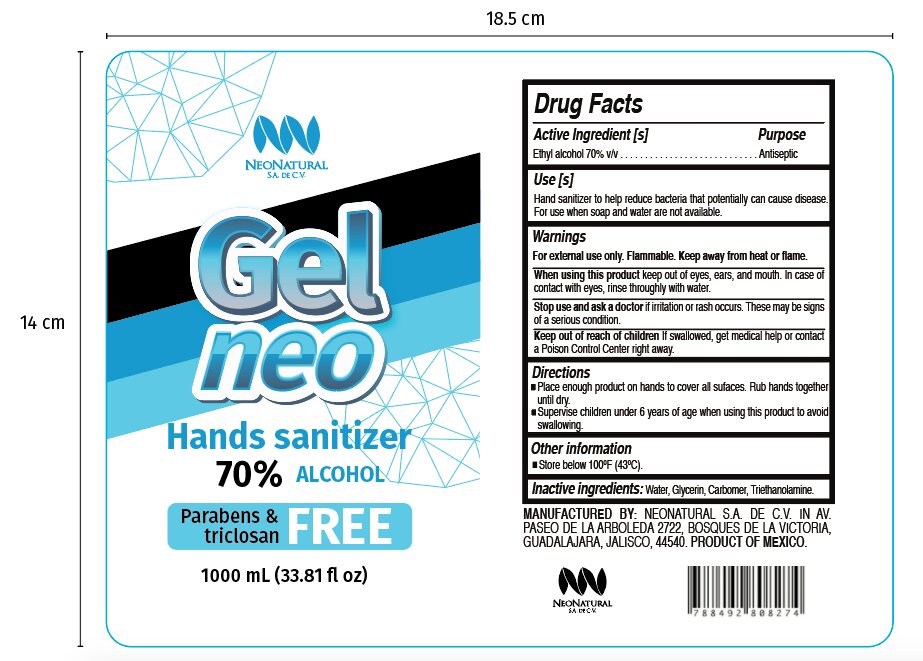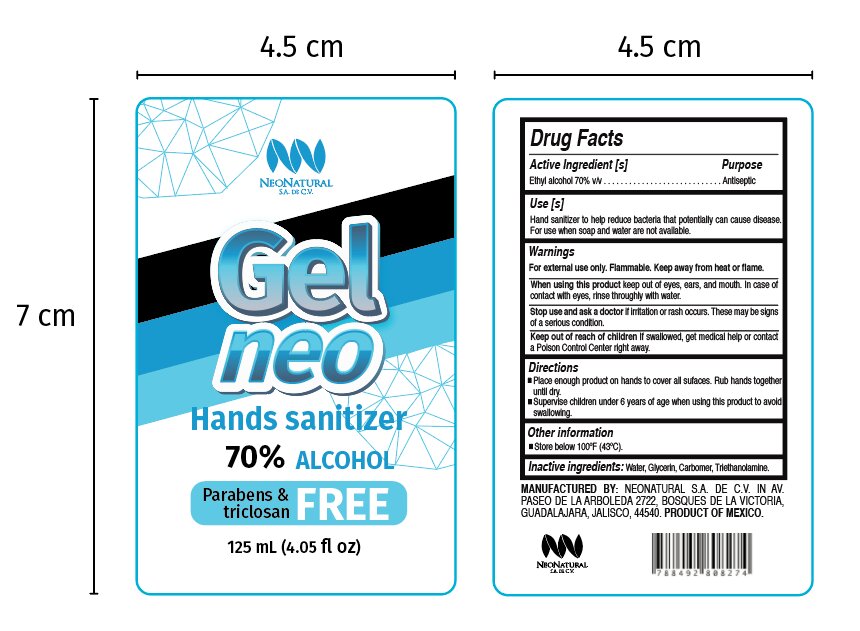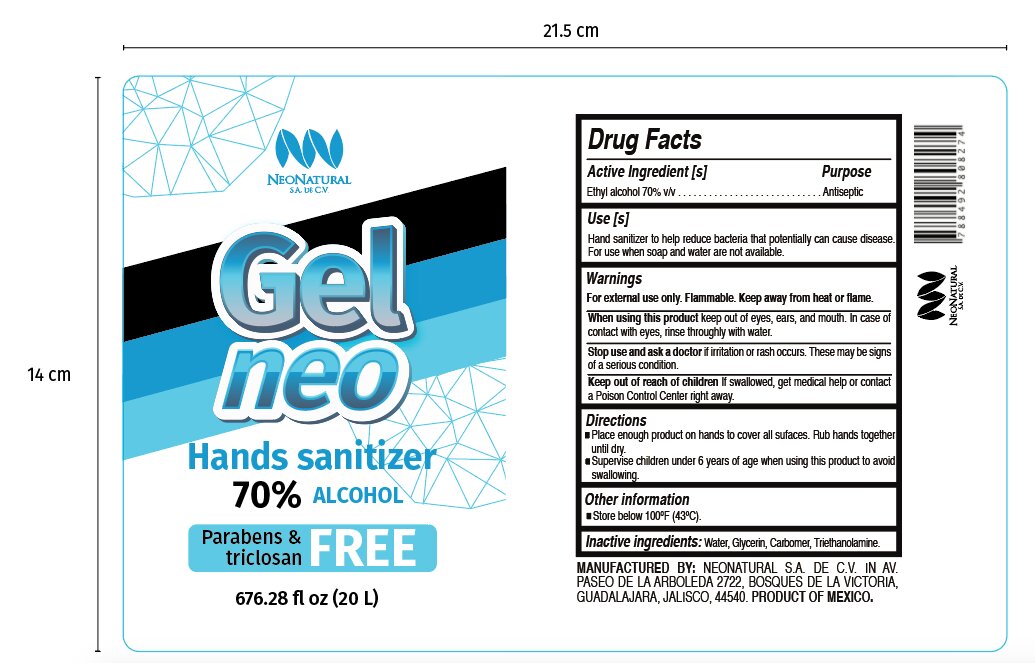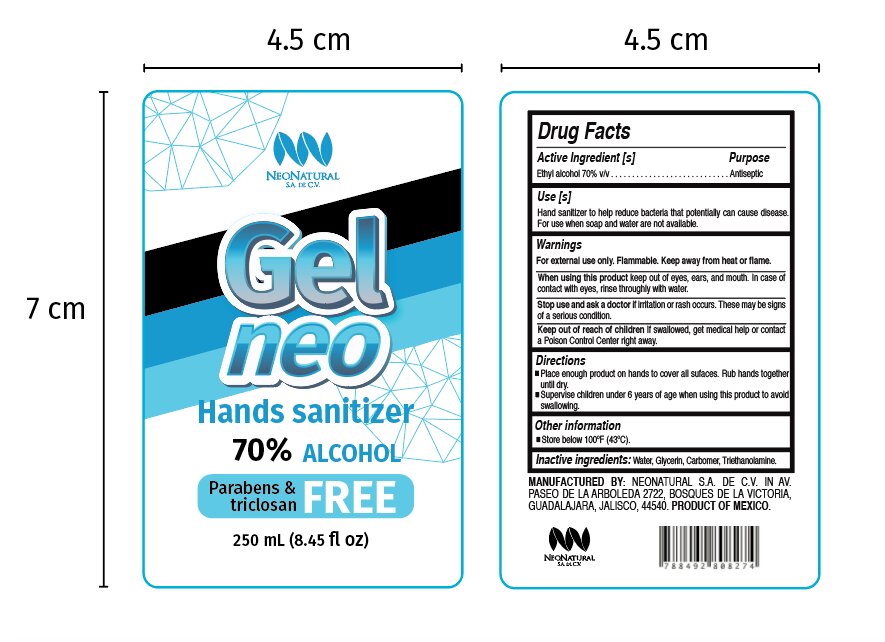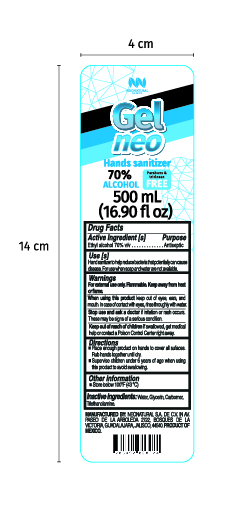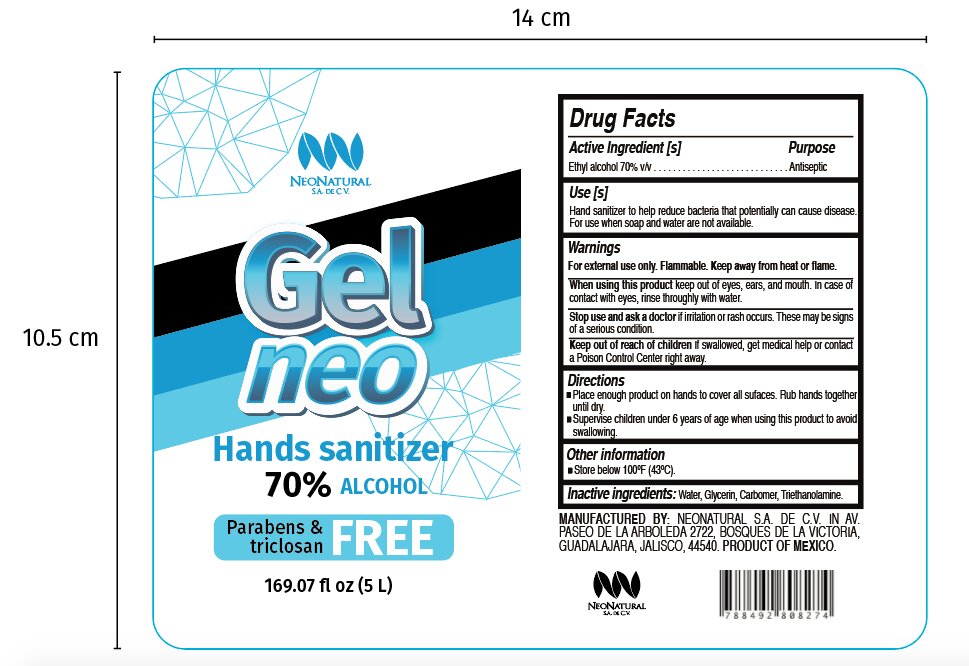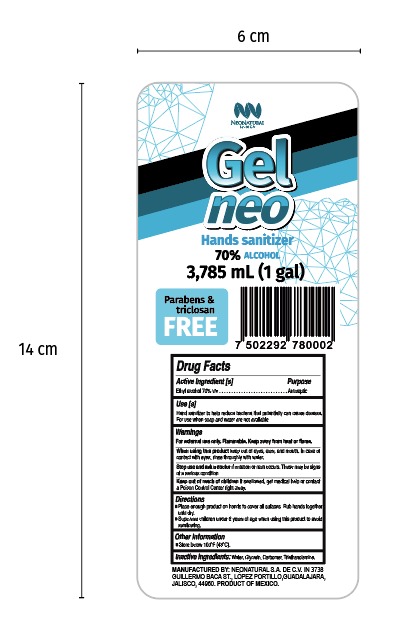 DRUG LABEL: Hand Sanitizer
NDC: 78103-001 | Form: GEL
Manufacturer: Neonatural SA de CV
Category: otc | Type: HUMAN OTC DRUG LABEL
Date: 20200723

ACTIVE INGREDIENTS: ALCOHOL 70 mL/100 mL
INACTIVE INGREDIENTS: GLYCERIN 2.4 mL/100 mL; TROLAMINE 0.27 mL/100 mL; WATER; CARBOMER 940 1.03 g/100 mL

Active Ingredient(s)

Alcohol 70% v/v. Purpose: Antiseptic

Purpose

Antiseptic, Hand Sanitizer

Use

Hand Sanitizer to help reduce bacteria that potentially can cause disease. For use when soap and water are not available.

Warnings

For external use only. Flammable. Keep away from heat or flame

Do not use

- in children less than 2 months of age
- on open skin wounds

When using this product keep out of eyes, ears, and mouth. In case of contact with eyes, rinse eyes thoroughly with water.
Stop use and ask a doctor if irritation or rash occurs. These may be signs of a serious condition.
Keep out of reach of children. If swallowed, get medical help or contact a Poison Control Center right away.

Stop use and ask a doctor if irritation or rash occurs. These may be signs of a serious condition.

Keep out of reach of children. If swallowed, get medical help or contact a Poison Control Center right away.

Directions

- Place enough product on hands to cover all surfaces. Rub hands together until dry.
- Supervise children under 6 years of age when using this product to avoid swallowing.

Other information

- Store below 100ºF (43ºC)

Inactive ingredients

water, glycerin, carbomer, triethanolamine

Package Label - Principal Display Panel

125 mL NDC: 78103-001-01

250 mL NDC: 78103-001-02

500 mL NDC: 78103-001-03

1000 mL NDC: 78103-001-04

5000 mL NDC: 78103-001-05

20000 mL NDC: 78103-001-06

3785 mL NDC: 78103-001-07